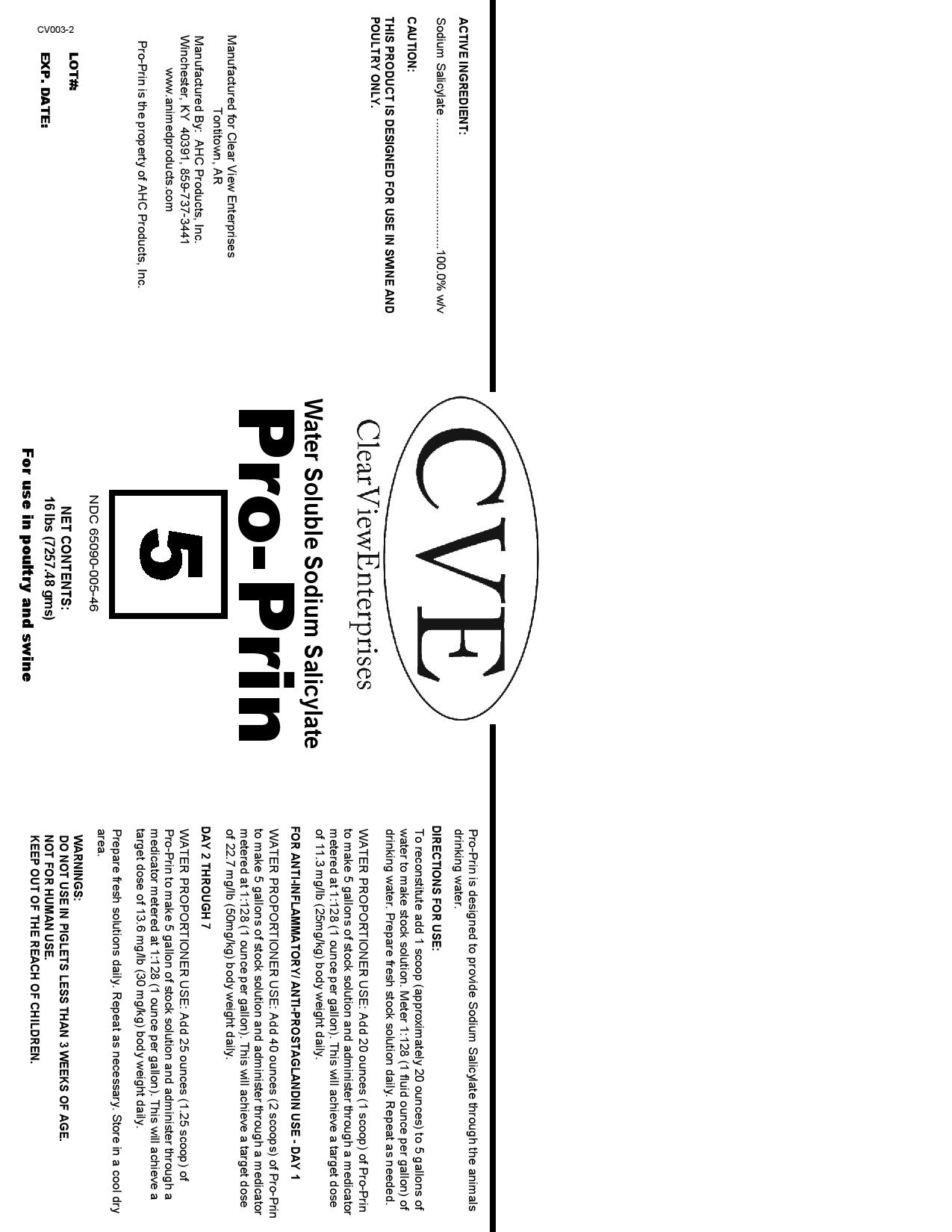 DRUG LABEL: Pro-Prin
NDC: 65090-005 | Form: GRANULE
Manufacturer: AHC Products Inc
Category: animal | Type: OTC ANIMAL DRUG LABEL
Date: 20200618

ACTIVE INGREDIENTS: SODIUM SALICYLATE 28.3 g/28.3 g

Pro-Prin

WARNINGS AND PRECAUTIONS

CAUTION:

THIS PRODUCT IS DESINGED FOR USE IN SWINE AND POULTRY ONLY.

WARNINGS:

DO NOT USE IN PIGLETS LESS THAN 3 WEEKS OF AGE

NOT FOR HUMAN USE

KEEP OUT OF THE REACH OF CHILDREN

INDICATIONS AND USAGE

Pro-Prin is designed to provide Sodium Salicylate through the animals drinking water.

DOSAGE AND ADMINISTRATION

To reconstitute add 1 scoop (approximately 20 ounces) to 5 gallons of water to make stock solution. Meter 1:128 (1 fluid ounce per gallon) of drinking water. Prepare fresh stock solution daily. Repeat as needed.

WATER PROPORTIONER USE: Add 20 ounces (1 scoop) of Pro-Prin to make 5 gallons of stock solution and administer through a medicator metered at 1:128 (1 ounce per gallon). THis will achieve a target does of 22.7 mg/lb (50 mg/kg) body weight daily.

FOR ANTI-INFLAMMATORY/ANTI-PROSTAGLANDIN USE - DAY 1

WATER PROPROPORTIONER USE: Add 40 ounces (2 scoops) of Pro-Prin to make 5 gallons of stock solution and administer through a medicator metered at 1:128 (1 ounce per gallon). This will achieve a target does of 22.7 mg/lb (50 mg/kg) body weight daily.

DAY 2 THROUGH 7

WATER PROPORTIONER USE: Add 25 ounces (1.25 scoop) of Pro-Prin to make 5 gallon of stock solution and administer through a medicator metered at 1:128 (1 ounce per gallon). This will achieve a target dose of 13.6 mg/lb (30 mg/kg) body weight daily.

ACTIVE INGREDIENT:

Sodium Salicylate 100.0% w/v

PACKAGE LABEL

CVE

ClearViewEnterprises

Water Soluble Sodium Salicylate

Pro-Prin

5

NDC 65090-005-46

NET CONTENTS: 16 lbs (7257.48 gms)

For use in poultry and swine